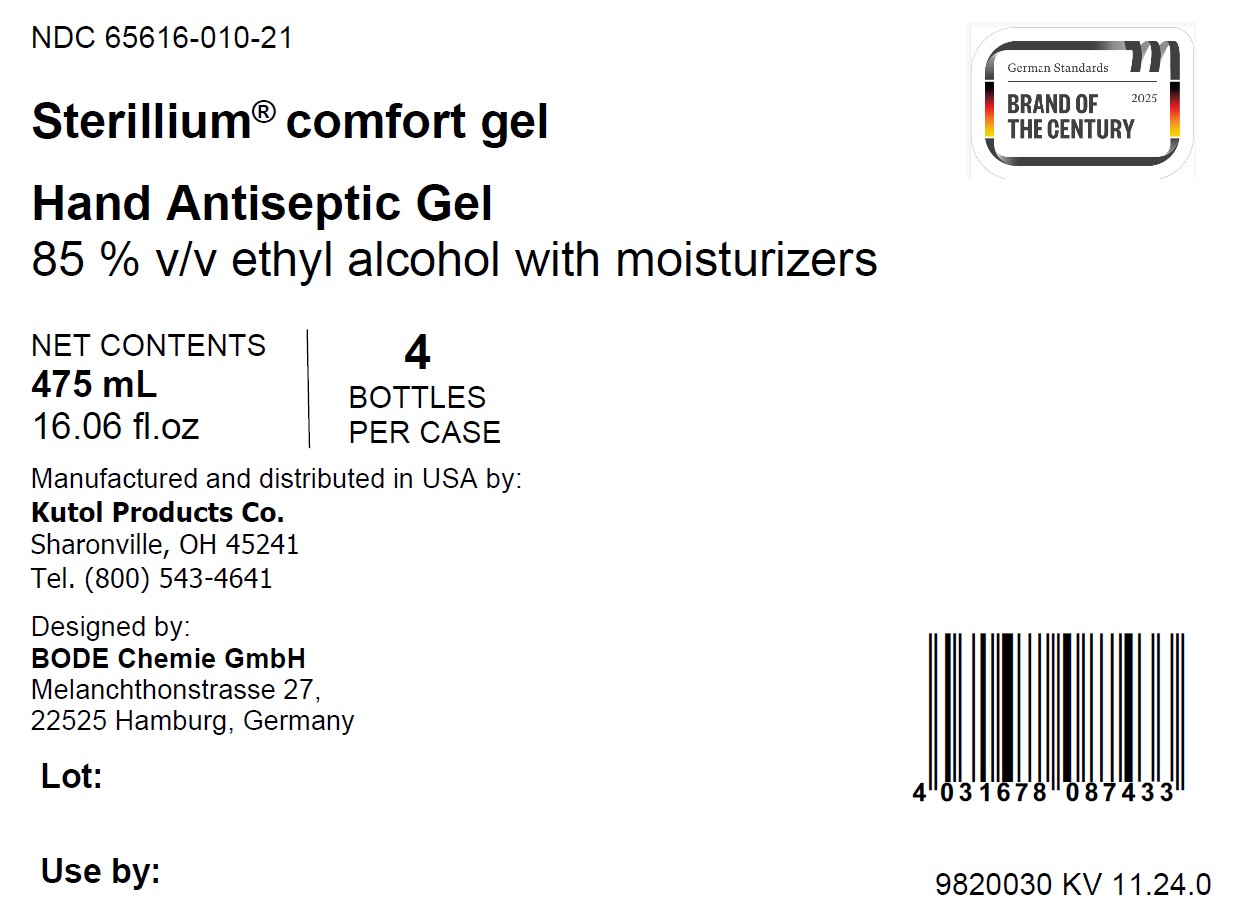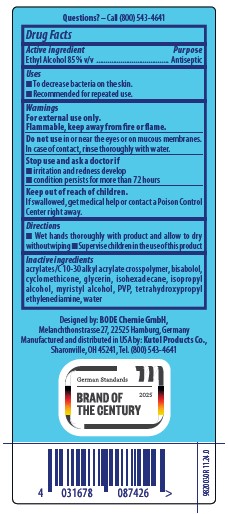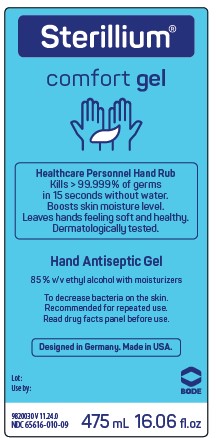 DRUG LABEL: Sterillium comfort
NDC: 65616-010 | Form: GEL
Manufacturer: BODE Chemie GmbH
Category: otc | Type: HUMAN OTC DRUG LABEL
Date: 20250203

ACTIVE INGREDIENTS: ALCOHOL 85 mL/100 mL
INACTIVE INGREDIENTS: ISOPROPYL ALCOHOL; GLYCERIN; MYRISTYL ALCOHOL; CYCLOMETHICONE; CARBOMER INTERPOLYMER TYPE A (55000 CPS); EDETOL; POVIDONE K90; WATER; ISOHEXADECANE; LEVOMENOL

65616-010

Active ingredient

Ethyl Alcohol 85 % v/v

Purpose

Antiseptic

Uses

• To decrease bacteria on the skin.

• Recommended for repeated use.

Warnings

For external use only.

Flammable, keep away from fire or flame.

Do not use in or near the eyes or on mucous membranes.

In case of contact, rinse thoroughly with water.

Stop use and ask a doctor if

• irritation and redness develop

• condition persists for more than 72 hours

Keep out of reach of children.

If swallowed, get medical help or contact a Poison Control Center right away.

Directions

• Wet hands thoroughly with product and allow to dry without wiping

• Supervise children in the use of this product

Inactive ingredients

acrylates/C 10-30 alkyl acrylate crosspolymer, bisabolol, cyclomethicone, glycerin, isohexadecane, isopropyl alcohol, myristyl alcohol, PVP, tetrahydroxypropyl ethylenediamine, water

PACKAGE LABEL

Sterillium

comfort gel

Healthcare personnel Hand Rub

Kills > 99.999% of germs

in 15 seconds without water.

Boosts skin moisture level.

Leaves hands feeling soft and healthy.

Dermatologically tested.

Hand Antiseptic Gel

85 % v/v ethyl alcohol with moisturizers

To decrease bacteria on the skin.

Recommended for repeated use.

Read drug facts panel before use.

Designed in Germany. Made in USA.

Lot:

Use by:

BODE

NDC 65616-010-09

475 mL 16.06 fl. oz